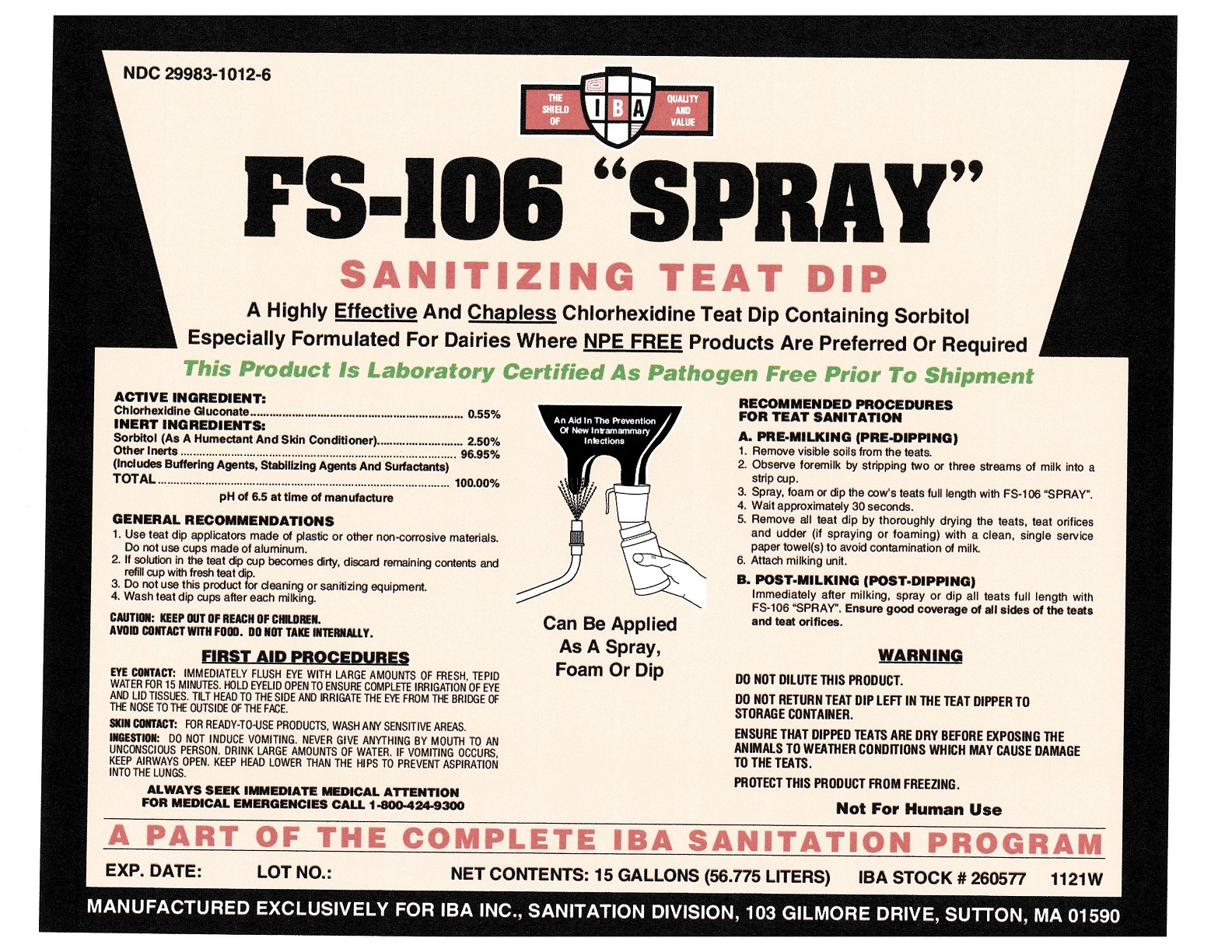 DRUG LABEL: FS-106Spray
NDC: 29983-1012 | Form: LIQUID
Manufacturer: IBA Inc.
Category: animal | Type: OTC ANIMAL DRUG LABEL
Date: 20251126

ACTIVE INGREDIENTS: CHLORHEXIDINE GLUCONATE 5.5 kg/100 kg

FS-106 Spray

ACTIVE INGREDIENT:

Chlorhexidine Gluconate.................................................................... 0.55%

INERT INGREDIENTS:

Sorbitol (As A Humectant And Skin Conditioner)............................ 2.50%
Other Inerts........................................................................................ 96.95%
(Includes Buffering Agents, Stabilizing Agents And Surfactants)
TOTAL............................................................................................. 100.00%
pH of 6.5 at time of manufacture

RECOMMENDED PROCEDURES FOR TEAT SANITATION

A. PRE-MILKING (PRE-DIPPING)
1. Remove visible soils from the teats.
2. Observe foremilk by stripping two or three streams of milk into a
strip cup.
3. Spray, foam or dip the cow’s teats full length with FS-106 “SPRAY”.
4. Wait approximately 30 seconds.
5. Remove all teat dip by thoroughly drying the teats, teat orifices
and udder (if spraying or foaming) with a clean, single service
paper towel(s) to avoid contamination of milk.
6. Attach milking unit.
B. POST-MILKING (POST-DIPPING)
Immediately after milking, spray or dip all teats full length with
FS-106 “SPRAY”. Ensure good coverage of all sides of the teats
and teat orifices.

GENERAL RECOMMENDATIONS
1. Use teat dip applicators made of plastic or other non-corrosive materials.
Do not use cups made of aluminum.
2. If solution in the teat dip cup becomes dirty, discard remaining contents and
refill cup with fresh teat dip.
3. Do not use this product for cleaning or sanitizing equipment.
4. Wash teat dip cups after each milking.

WARNING

DO NOT DILUTE THIS PRODUCT.
DO NOT RETURN TEAT DIP LEFT IN THE TEAT DIPPER TO
STORAGE CONTAINER.
ENSURE THAT DIPPED TEATS ARE DRY BEFORE EXPOSING THE ANIMALS TO WEATHER CONDITIONS WHICH MAY CAUSE DAMAGE
TO THE TEATS.
PROTECT THIS PRODUCT FROM FREEZING.
Not For Human Use.

CAUTION: KEEP OUT OF REACH OF CHILDREN.
AVOID CONTACT WITH FOOD. DO NOT TAKE INTERNALLY.

FIRST AID PROCEDURES

EYE CONTACT: IMMEDIATELY FLUSH EYE WITH LARGE AMOUNTS OF FRESH, TEPID WATER FOR 15 MINUTES. HOLD EYELID OPEN TO ENSURE COMPLETE IRRIGATION OF EYE AND LID TISSUES. TILT HEAD TO THE SIDE AND IRRIGATE THE EYE FROM THE BRIDGE OF THE NOSE TO THE OUTSIDE OF THE FACE.
SKIN CONTACT: FOR READY-TO-USE PRODUCTS, WASH ANY SENSITIVE AREAS.
INGESTION: DO NOT INDUCE VOMITING. NEVER GIVE ANYTHING BY MOUTH TO AN UNCONSCIOUS PERSON. DRINK LARGE AMOUNTS OF WATER. IF VOMITING OCCURS, KEEP AIRWAYS OPEN. KEEP HEAD LOWER THAN THE HIPS TO PREVENT ASPIRATION INTO THE LUNGS.
ALWAYS SEEK IMMEDIATE MEDICAL ATTENTION
FOR MEDICAL EMERGENCIES CALL 1-800-424-9300